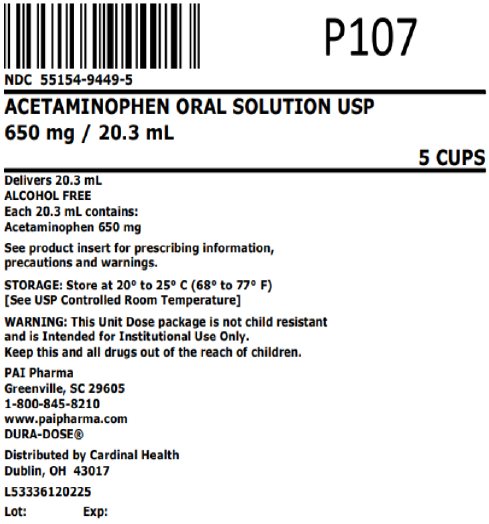 DRUG LABEL: Acetaminophen
NDC: 55154-9449 | Form: SOLUTION
Manufacturer: Cardinal Health 107, LLC
Category: otc | Type: HUMAN OTC DRUG LABEL
Date: 20250307

ACTIVE INGREDIENTS: ACETAMINOPHEN 650 mg/20.3 mL
INACTIVE INGREDIENTS: ANHYDROUS CITRIC ACID; FD&C RED NO. 40; GLYCERIN; POLYETHYLENE GLYCOL, UNSPECIFIED; PROPYLENE GLYCOL; WATER; SODIUM BENZOATE; SODIUM CITRATE, UNSPECIFIED FORM; SORBITOL; SUCROSE

Acetaminophen Oral Solution USP
Alcohol Free

Active ingredient (in each 5 mL teaspoonful)

ACETAMINOPHEN 160 mg

Purpose

Pain reliever/fever reducer

Uses

temporarily relieves minor aches and pains due to:

- headache
- muscular aches
- backache
- minor pain of arthritis
- the common cold
- toothache
- premenstrual and menstrual cramps

temporarily reduces fever

Warnings

Liver warning: This product contains acetaminophen. Severe liver damage may occur if:

- adult takes more than 6 doses in 24 hours, which is the maximum daily amount
- child takes more than 5 doses in 24 hours
- taken with other drugs containing acetaminophen
- adult has 3 or more alcoholic drinks every day while using this product

Allergy alert: Acetaminophen may cause severe skin reactions. Symptoms may include:

- skin reddening
- blisters
- rash

If a skin reaction occurs, stop use and seek medical help right away.

Sore throat warning: If sore throat is severe, persists for more than 2 days, is accompanied or followed by fever, headache, rash, nausea, or vomiting, consult a doctor promptly.

Do not use

- with any other drug containing acetaminophen (prescription or nonprescription).
- if you are not sure whether a drug contains acetaminophen, ask a doctor or pharmacist.
- for more than 10 days for pain unless directed by a doctor
- for more than 3 days for fever unless directed by a doctor
- if you are allergic to acetaminophen or any of the inactive ingredients of this product

Ask a doctor before use if the user has liver disease

Ask a doctor or pharmacist before use if the user is taking the blood thining drug warfarin.

Stop use and ask a doctor if

- symptoms do not improve
- new symptoms occur
- pain or fever persists or gets worse

PREGNANCY OR BREAST FEEDING

If pregnant or breast-feeding, ask a health professional before use.

Keep out of reach of children.

Overdose warning: Taking more than the recommended dose (overdose) may cause liver damage. In case of overdose, get medical help or contact a Poison Control Center right away. (1-800-222-1222). Quick medical attention is critical for adults as well as children even if you do not notice any signs or symptoms.

WARNING:

This Unit Dose package is not child resistant and is Intended for Institutional Use Only. Keep this and all drugs out of the reach of children.

Directions

- do not take more than directed (see overdose warning)

age | dose
adults and children 12 years of age and over | 20.3 mL (650 mg) every 4 to 6 hours not to exceed 6 doses in a 24-hour period
children 6 to under 12 years of age | 10.15 mL (325 mg) every 4 hours not to exceed 5 doses in a 24-hour period
children 4 to under 6 years of age | 7.5 mL (240 mg) every 4 hours not to exceed 5 doses in a 24-hour period
children 2 to under 4 years of age | 5 mL (160 mg) every 4 hours not to exceed 5 doses in a 24-hour period
children under 2 years of age | consult a doctor

Other information

■ Each 5 mL contains: sodium 2 mg

■ store at 20° to 25°C (68° to 77°F). [See USP Controlled Room Temperature]

■ keep tightly closed ■ protect from light

■ a red, cherry flavored solution supplied in the following oral dosage forms:

Overbagged with 5 x 20.3 mL unit dose cups per bag, NDC 55154-9449-5

Inactive ingredients:

Citric acid, FD&C Red No. 40, flavoring, glycerin, polyethylene glycol, propylene glycol, purified water, sodium benzoate, sodium citrate, sorbitol and sucrose.

Questions or comments?

Call 1-800-845-8210. You may also report serious side effects to this phone number.

MANUFACTURED BY:

Pharmaceutical Associates, Inc.

Greenville, SC 29605

www.paipharma.com

Distributed By:

Cardinal Health

Dublin, OH 43017

L53336120225

R10/20

Principal Display Panel

NDC 55154-9449-5

ACETAMINOPHEN ORAL SOLUTION USP

650 mg / 20.3 mL

5 CUPS